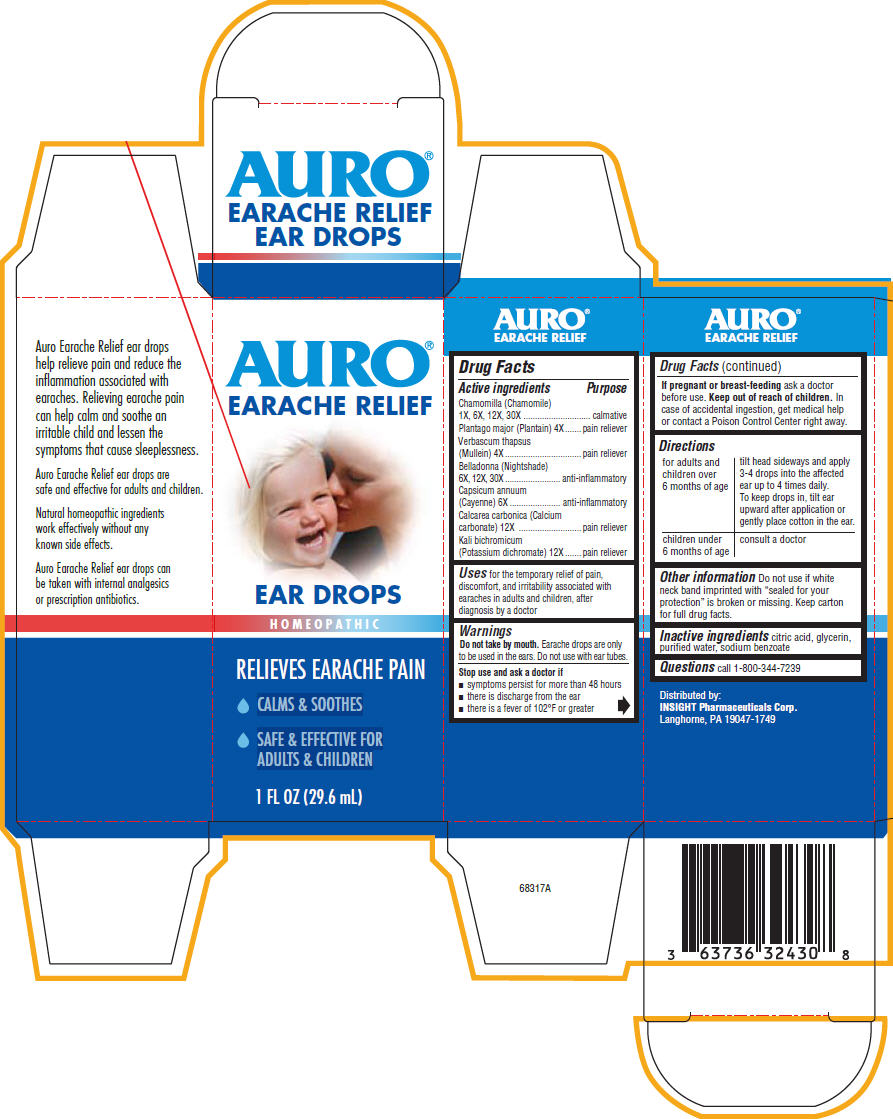 DRUG LABEL: Auro Earache Relief
NDC: 63736-324 | Form: LIQUID
Manufacturer: Insight Pharmaceuticals
Category: homeopathic | Type: HUMAN OTC DRUG LABEL
Date: 20100623

ACTIVE INGREDIENTS: MATRICARIA RECUTITA 4 mL/30 mL; PLANTAGO MAJOR 0.3256 mL/30 mL; VERBASCUM THAPSUS 0.3256 mL/30 mL; ATROPA BELLADONNA 0.3256 mL/30 mL; CHILI PEPPER 0.3256 mL/30 mL; OYSTER SHELL CALCIUM CARBONATE, CRUDE 0.3256 mL/30 mL; POTASSIUM DICHROMATE 0.3256 mL/30 mL
INACTIVE INGREDIENTS: CITRIC ACID MONOHYDRATE; GLYCERIN; WATER; SODIUM BENZOATE

AURO®
EARACHE RELIEF
EAR DROPS

Drug Facts

ACTIVE INGREDIENT

Active ingredients | Purpose
Chamomilla (Chamomile) 1X, 6X, 12X, 30X | calmative
Plantago major (Plantain) 4X | pain reliever
Verbascum thapsus (Mullein) 4X | pain reliever
Belladonna (Nightshade) 6X, 12X, 30X | anti-inflammatory
Capsicum annuum (Cayenne) 6X | anti-inflammatory
Calcarea carbonica (Calcium carbonate) 12X | pain reliever
Kali bichromicum (Potassium dichromate) 12X | pain reliever

Uses

for the temporary relief of pain, discomfort, and irritability associated with earaches in adults and children, after diagnosis by a doctor

Warnings

Do not take by mouth. Earache drops are only to be used in the ears. Do not use with ear tubes.

Stop use and ask a doctor if

- symptoms persist for more than 48 hours
- there is discharge from the ear
- there is a fever of 102°F or greater

PREGNANCY OR BREAST FEEDING

If pregnant or breast-feeding ask a doctor before use.

Keep out of reach of children. In case of accidental ingestion, get medical help or contact a Poison Control Center right away.

Directions

for adults and children over 6 months of age | tilt head sideways and apply 3-4 drops into the affected ear up to 4 times daily. To keep drops in, tilt ear upward after application or gently place cotton in the ear.
children under 6 months of age | consult a doctor

Other information

Do not use if white neck band imprinted with "sealed for your protection" is broken or missing. Keep carton for full drug facts.

Inactive ingredients

citric acid, glycerin, purified water, sodium benzoate

Questions

call 1-800-344-7239

Distributed by:
INSIGHT Pharmaceuticals Corp.
Langhorne, PA 19047-1749

PRINCIPAL DISPLAY PANEL - 29.6 mL Bottle Carton

AURO®
EARACHE RELIEF

EAR DROPS

HOMEOPATHIC

RELIEVES EARACHE PAIN

- CALMS & SOOTHES
- SAFE & EFFECTIVE FOR
  ADULTS & CHILDREN

1 FL OZ (29.6 mL)